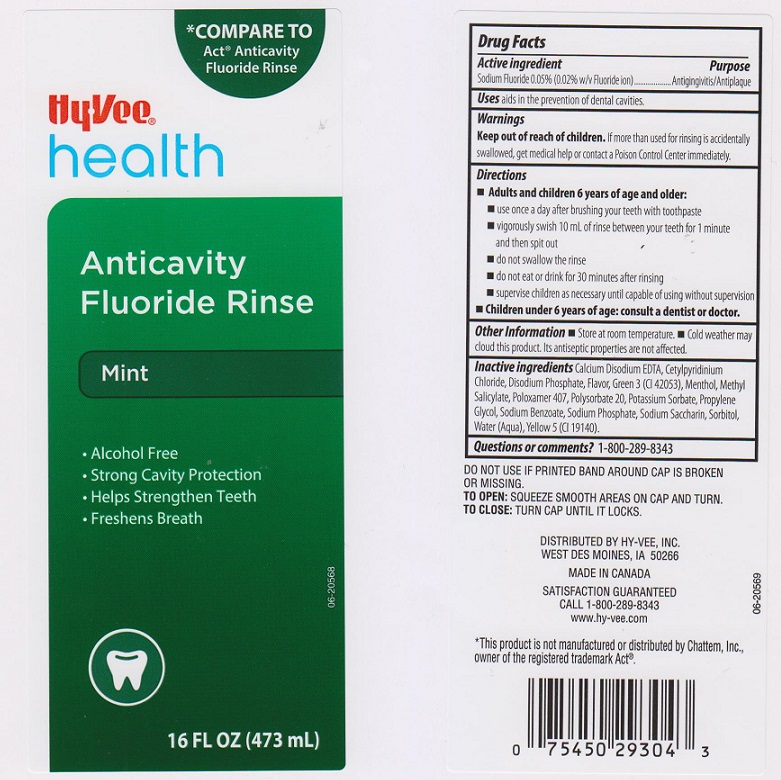 DRUG LABEL: HYVEE
NDC: 42507-554 | Form: LIQUID
Manufacturer: HYVEE INC.
Category: otc | Type: HUMAN OTC DRUG LABEL
Date: 20151130

ACTIVE INGREDIENTS: SODIUM FLUORIDE 0.5 mg/1 mL
INACTIVE INGREDIENTS: WATER; SORBITOL; PROPYLENE GLYCOL; SODIUM PHOSPHATE; POLYSORBATE 20; POLOXAMER 407; SODIUM BENZOATE; POTASSIUM SORBATE; EDETATE CALCIUM DISODIUM ANHYDROUS; SODIUM PHOSPHATE, DIBASIC, ANHYDROUS; SACCHARIN SODIUM; CETYLPYRIDINIUM CHLORIDE; MENTHOL; METHYL SALICYLATE; FD&C GREEN NO. 3; FD&C YELLOW NO. 5

DRUG FACTS

Active ingredient

Sodium Fluoride 0.05% (0.02% w/v Fluoride ion)

Purpose

Antigingivitis/Antiplaque

Uses

aids in the prevention of dental cavities

Warnings

Keep out of reach of children

Keep out of reach of children.

If more than used for rinsin is accidentally swallowed, get medical help or contact a Poison Control Center immediately.

Directions

- Adults and children 6 years of age and older:
- use once a day after brushing your teeth with toothpaste
- vigorously swish 10 mL of rinse between your teeth for 1 minute and then spit out
- do not swallow the rinse
- do not eat or drink for 30 minutes after rinsing
- supervise children as necessary until capable of using without supervision
- Children under 6 years of age: consult a dentist or doctor.

Other information

- Store at room temperature
- Cold weather may cloud this product. Its antiseptic properties are not affected.

Inactive ingredients

Calcium Disodium EDTA, Cetylpyridinium Chloride, Disodium Phosphate, Flavor, Green 3 (CI 42053), Menthol, Methyl Salicylate, Poloxamer 407, Polysorbate 20, Potassium Sorbate, Propylene Glycol, Sodium Benzoate, Sodium Phosphate, Sodium Saccharin, Sorbitol, Water (Aqua), Yellow 5 (CI 19140).

Questions or comments?

1-800-289-8343